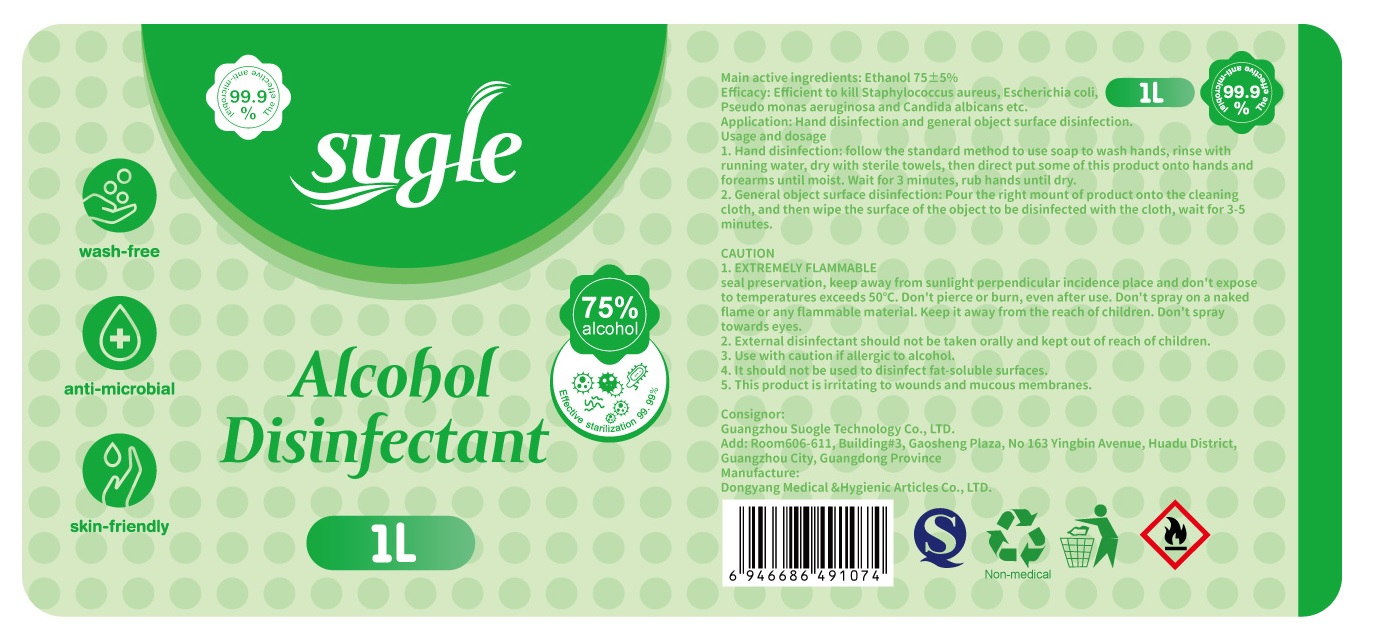 DRUG LABEL: 75% ALCOHOL DISINFECTANT
NDC: 81276-016 | Form: LIQUID
Manufacturer: Dongyang Medical & Hygienic Articles Co., Ltd.
Category: otc | Type: HUMAN OTC DRUG LABEL
Date: 20201227

ACTIVE INGREDIENTS: ALCOHOL 750 mL/1 L
INACTIVE INGREDIENTS: WATER

81276-016 1L DONGYANG MEDICAL

This is a hand sanitizer manufactured according to the Temporary Policy for Preparation of Certain Alcohol-Based Hand Sanitizer Products During the Public Health Emergency (CoViD-19); Guidance for Industry.

The hand sanitizer is manufactured using only the following United States Pharmacopoeia (USP) grade ingredients in the preparation of the product (percentage in final product formulation) consistent with World Health Organization (WHO) recommendations:

1. Alcohol (ethanol) (USP or Food Chemical Codex (FCC) grade) (80%, volume/volume (v/v)) in an aqueous solution denatured according to Alcohol and Tobacco Tax and Trade Bureau regulations in 27 CFR part 20.
2. Glycerol (1.45% v/v).
3. Hydrogen peroxide (0.125% v/v).
4. Sterile distilled water or boiled cold water.

The firm does not add other active or inactive ingredients. Different or additional ingredients may impact the quality and potency of the product.

Active Ingredient(s)

Alcohol 75% v/v. Purpose: Antiseptic,Disinfection

Purpose

Efficacy:

Efficient to kill Staphylococcus aureus,Escherichia coil,Pseudo monas aeruginosa and Candida alibicans etc.

Application:

Hand disinfection and general object surface disinfection.

Use

1.Hand disinfection follow the standard method to use soap to wash hands,rinse with running water,dry with sterile towels,then direct spray this product on hands and forearms until moist.wait for 3 minutes,rub hands until dry.

2.General object surface disinfection directly spray on the object surface for until moist,wait for 3-5 minutes.

Warnings

1.EXTREMELY FLAMMABLE:

seal preservation, keep away from sunlight perpendicular incidence place and don't expose to temperatures exceeds 50℃.Don't pierce or burn, even after use. Don't spray on a naked flame or any flammable material. Keep it away from the reach of children. Don't spray towards eyes.

2.External disinfectant should not be taken orally and kept out of reach of children.

3.Use with caution if allergic to alcohol.

4.It should not be used to disinfect fat-soluble surfaces.

5.This product is irritating to wounds and mucous membranes.

Do not use

- in children less than 2 months of age
- on open skin wounds

When using this product keep out of eyes, ears, and mouth. In case of contact with eyes, rinse eyes thoroughly with water.
Stop use and ask a doctor if irritation or rash occurs. These may be signs of a serious condition.
Keep out of reach of children. If swallowed, get medical help or contact a Poison Control Center right away.

Stop use and ask a doctor if irritation or rash occurs. These may be signs of a serious condition.

Keep out of reach of children. If swallowed, get medical help or contact a Poison Control Center right away.

Directions

1.Hand disinfection follow the standard method to use soap to wash hands,rinse with running water,dry with sterile towels,then direct spray this product on hands and forearms until moist.wait for 3 minutes,rub hands until dry.

2.General object surface disinfection directly spray on the object surface for until moist,wait for 3-5 minutes.

Other information

- Store between 15-30C (59-86F)
- Avoid freezing and excessive heat above 50C (104F)

Inactive ingredients

purified water USP

Package Label - Principal Display Panel

1L NDC: 81276-016-01